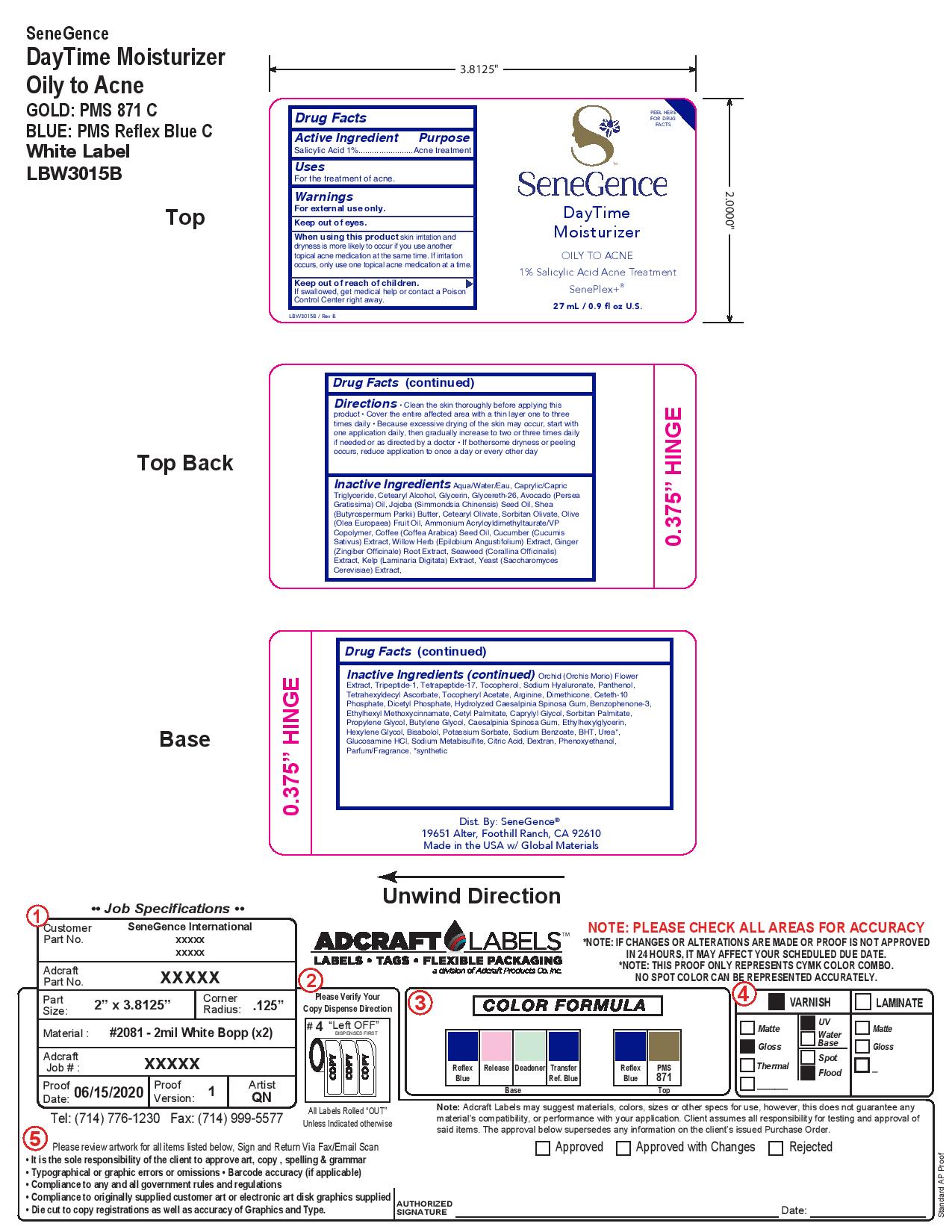 DRUG LABEL: DayTime Moisturizer
NDC: 72644-633 | Form: LOTION
Manufacturer: SGII, INC
Category: otc | Type: HUMAN OTC DRUG LABEL
Date: 20200916

ACTIVE INGREDIENTS: SALICYLIC ACID 1 g/100 g
INACTIVE INGREDIENTS: SODIUM BENZOATE; SODIUM METABISULFITE; GINGER; CETETH-10 PHOSPHATE; LEVOMENOL; LAMINARIA DIGITATA; TOCOPHEROL; PANTHENOL; TETRAHEXYLDECYL ASCORBATE; .ALPHA.-TOCOPHEROL ACETATE; DIHEXADECYL PHOSPHATE; CAESALPINIA SPINOSA RESIN; CETYL PALMITATE; OCTINOXATE; OLIVE OIL; YEAST, UNSPECIFIED; PREZATIDE; BUTYLENE GLYCOL; HEXYLENE GLYCOL; POTASSIUM SORBATE; BUTYLATED HYDROXYTOLUENE; CETOSTEARYL ALCOHOL; SHEA BUTTER; HYALURONATE SODIUM; WATER; MEDIUM-CHAIN TRIGLYCERIDES; AVOCADO OIL; AMMONIUM ACRYLOYLDIMETHYLTAURATE/VP COPOLYMER; GLYCERIN; GLYCERETH-26; JOJOBA OIL; CETEARYL OLIVATE; SORBITAN OLIVATE; CUCUMBER JUICE; ARGININE; CAPRYLYL GLYCOL; ETHYLHEXYLGLYCERIN; UREA; GLUCOSAMINE HYDROCHLORIDE; CITRIC ACID MONOHYDRATE; DEXTRAN 1; PHENOXYETHANOL; ARABICA COFFEE OIL; EPILOBIUM ANGUSTIFOLIUM FLOWERING TOP; CORALLINA OFFICINALIS; ANACAMPTIS MORIO FLOWER; DIMETHICONE; OXYBENZONE; SORBITAN MONOPALMITATE; PROPYLENE GLYCOL; FRAGRANCE CLEAN ORC0600327

Daytime Moisturizer

Active Ingredients

Salicylic Acid 1%

Purpose

Salicylic Acid 1%.......Acne Treatment

Uses

For the treatment of acne.

Warnings

For external use only.

Keep out of eyes

When using this product skin irritation and dryness is more likely to occur if you use another
topical acne medication at the same time. If irritation occurs, only use one topical acne medication at a time

Keep out of reach of children. If swallowed, get medical help or contact a Poison Control Center right away.

Directions

Clean the skin thoroughly before applying this product

• Cover the entire affected area with a thin layer one to three times daily

• Because excessive drying of the skin may occur, start with one application daily, then gradually increase to two or three times daily
if needed or as directed by a doctor

• If bothersome dryness or peeling occurs, reduce application to once a day or every other day

Inactive Ingredients

Aqua/Water/Eau, Caprylic/CapricTriglyceride, Cetearyl Alcohol, Glycerin, Glycereth-26, Avocado (Perse
Gratissima) Oil, Jojoba (Simmondsia Chinensis) Seed Oil, Shea (Butyrospermum Parkii) Butter, Cetearyl Olivate, Sorbitan Olivate, Oliv
(Olea Europaea) Fruit Oil, Ammonium Acryloyldimethyltaurate/VP Copolymer, Coffee (Coffea Arabica) Seed Oil, Cucumber (Cucumis
Sativus) Extract, Willow Herb (Epilobium Angustifolium) Extract, Ginge (Zingiber Officinale) Root Extract, Seaweed (Corallina Officinalis) Extract, Kelp (Laminaria Digitata) Extract, Yeast (Saccharomyces Cerevisiae) Extract,

Orchid (Orchis Morio) Flower Extract, Tripeptide-1, Tetrapeptide-17, Tocopherol, Sodium Hyaluronate, Panthenol, Tetrahexyldecyl Ascorbate, Tocopheryl Acetate, Arginine, Dimethicone, Ceteth-10 Phosphate, Dicetyl Phosphate, Hydrolyzed Caesalpinia Spinosa Gum, Benzophenone-3, Ethylhexyl Methoxycinnamate, Cetyl Palmitate, Caprylyl Glycol, Sorbitan Palmitate, Propylene Glycol, Butylene Glycol, Caesalpinia Spinosa Gum, Ethylhexylglycerin, Hexylene Glycol, Bisabolol, Potassium Sorbate, Sodium Benzoate, BHT, Urea*, Glucosamine HCl, Sodium Metabisulfite, Citric Acid, Dextran, Phenoxyethanol, Parfum/Fragrance. *synthetic